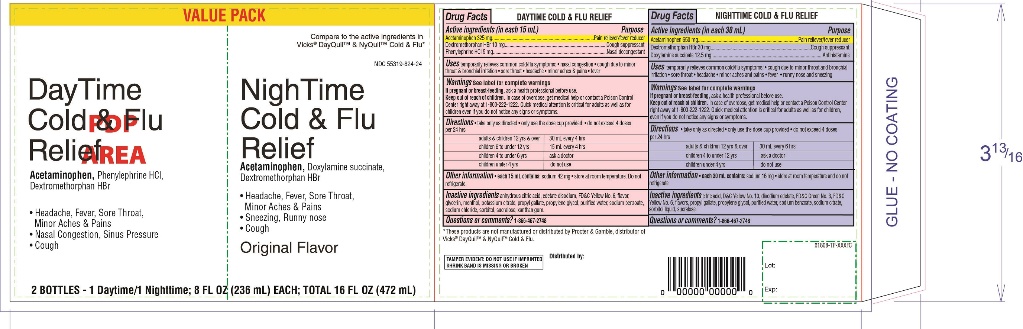 DRUG LABEL: Family Dollar Daytime and Nighttime Combo Pack
NDC: 55319-808 | Form: KIT | Route: ORAL
Manufacturer: FAMILY DOLLAR SERVICES INC
Category: otc | Type: HUMAN OTC DRUG LABEL
Date: 20230908

ACTIVE INGREDIENTS: ACETAMINOPHEN 325 mg/15 mL; DEXTROMETHORPHAN HYDROBROMIDE 10 mg/15 mL; PHENYLEPHRINE HYDROCHLORIDE 5 mg/15 mL; ACETAMINOPHEN 650 mg/30 mL; DEXTROMETHORPHAN HYDROBROMIDE 30 mg/30 mL; DOXYLAMINE SUCCINATE 12.5 mg/30 mL
INACTIVE INGREDIENTS: ANHYDROUS CITRIC ACID; EDETATE DISODIUM; FD&C YELLOW NO. 6; GLYCERIN; MENTHOL, UNSPECIFIED FORM; POTASSIUM CITRATE; PROPYL GALLATE; PROPYLENE GLYCOL; WATER; SODIUM BENZOATE; SODIUM CHLORIDE; SORBITOL; SUCRALOSE; XANTHAN GUM; ANHYDROUS CITRIC ACID; D&C YELLOW NO. 10; EDETATE DISODIUM; FD&C GREEN NO. 3; FD&C YELLOW NO. 6; PROPYL GALLATE; PROPYLENE GLYCOL; WATER; SODIUM BENZOATE; SODIUM CITRATE, UNSPECIFIED FORM; SORBITOL; SUCRALOSE

Family Dollar Daytime & Nighttime Combo Pack Cold & Flu

FAMILY DOLLAR DAYTIME COLD & FLU RELIEF

Active ingredients (in each 15 mL)

Acetaminophen 325 mg
Dextromethorphan HBr 10 mg
Phenylephrine HCl 5 mg

Purpose

Pain reliever/Fever reducer
Cough suppressant
Nasal decongestant

Uses

temporarily relieves common cold/flu symptoms:

- nasal congestion
- cough due to minor throat & bronchial irritation
- minor aches & pains
- headache
- fever
- sore throat

Warnings

PREGNANCY OR BREAST FEEDING

If pregnant or breast-feeding, ask a health professional before use.

Keep out of reach of children. In case of overdose, get medical help or contact a Poison Control Center right away. Quick medical attention is critical for adults as well as for children even if you do not notice any signs or symptoms.

Directions

- take only as directed
- Only use the dose cup provided
- do not exceed 4 doses per 24 hrs

adults & children 12 yrs & over | 30 mL every 4 hours
Children 6 to under 12 yrs | 15 mL every 4 hours
children 4 to under 12 yrs | ask a doctor
children under 4 yrs | do not use

Other information

each 15 mL contains:

- sodium 42 mg
- store at room temperature
- Do not refrigerate.

Inactive ingredients

Anhydrous citric acid, disodium edetate, FD&C Yellow No. 6, flavor, glycerin, menthol, potassium citrate, propyl gallate, purified water, sodium benzoate, sodium chloride, sorbitol, sucralose, xanthan gum

Questions?

1-866-467-2748

FAMILY DOLLAR NIGHTTIME COLD & FLU RELIEF

Active ingredients (in each 30 mL)

Acetaminophen 650 mg
Dextromethorphan HBr 30 mg
Doxylamine succinate 12.5 mg

Purpose

Pain reliever/Fever reducer
Cough suppressant
Antihistamine

Uses

temporarily relieves common cold/flu symptoms:

- cough due to minor throat & bronchial irritation
- minor aches & pains
- headache
- fever
- sore throat
- runny nose & sneezing

Warnings

PREGNANCY OR BREAST FEEDING

If pregnant or breast-feeding, ask a health professional before use.

Keep out of reach of children. In case of overdose, get medical help or contact a Poison Control Center right away. Quick medical attention is critical for adults as well as for children even if you do not notice any signs or symptoms.

Directions

- take only as directed
- Only use the dose cup provided
- do not exceed 4 doses per 24 hrs

adults & children 12 yrs & over | 30 mL every 4 hours
children 4 to under 12 yrs | ask a doctor
children under 4 yrs | do not use

Other information

- each 30 mL contains: sodium 16 mg
- Store at room temperature
- Do not refrigerate

Inactive ingredients

Citric acid, D&C Yellow No. 10, disodium edetate, FD&C Green No.3, FD&C Yellow no 6, flavor, propyl gallate, propylene glycol, purified water, sodium benzoate, sodium citrate, sorbitol, sucralose

Questions?

1-866-467-2748

Distributed By:

PRINCIPAL DISPLAY PANEL - Kit Carton

Compare to the active ingredients in Vicks®DayQuil™ & NyQuil™ Cold & Flu*

NDC# 55319-808-16

DayTime

Cold & Flu

Relief

Acetaminophen, Dextromethorphan HBr,

Phenylephrine HCl

- Headache, Fever, Sore Throat, Minor Aches & Pains
- Nasal Congestion & Sinus Pressure
- Cough

NightTime

Cold & Flu

Relief

Acetaminophen, Dextromethorphan HBr

Dextromethorphan HBr

- headache, Fever, Sore Throat,
Minor Aches & Pains

Original Flavor

TAMPER EVIDENT: DO NOT USE IF IMPRINTED SHRINK BAND IS MISSING OR BROKEN.

2 BOTTLES – 1 Daytime/1Nighttime; 8 FL OZ (236 mL) Each; TOTAL 16 FL OZ (472 mL)

*These product is not manufactured or distributed by Procter & Gamble, distributor of Vicks®Dayquil™ & Nyquil™ Cold & flu.